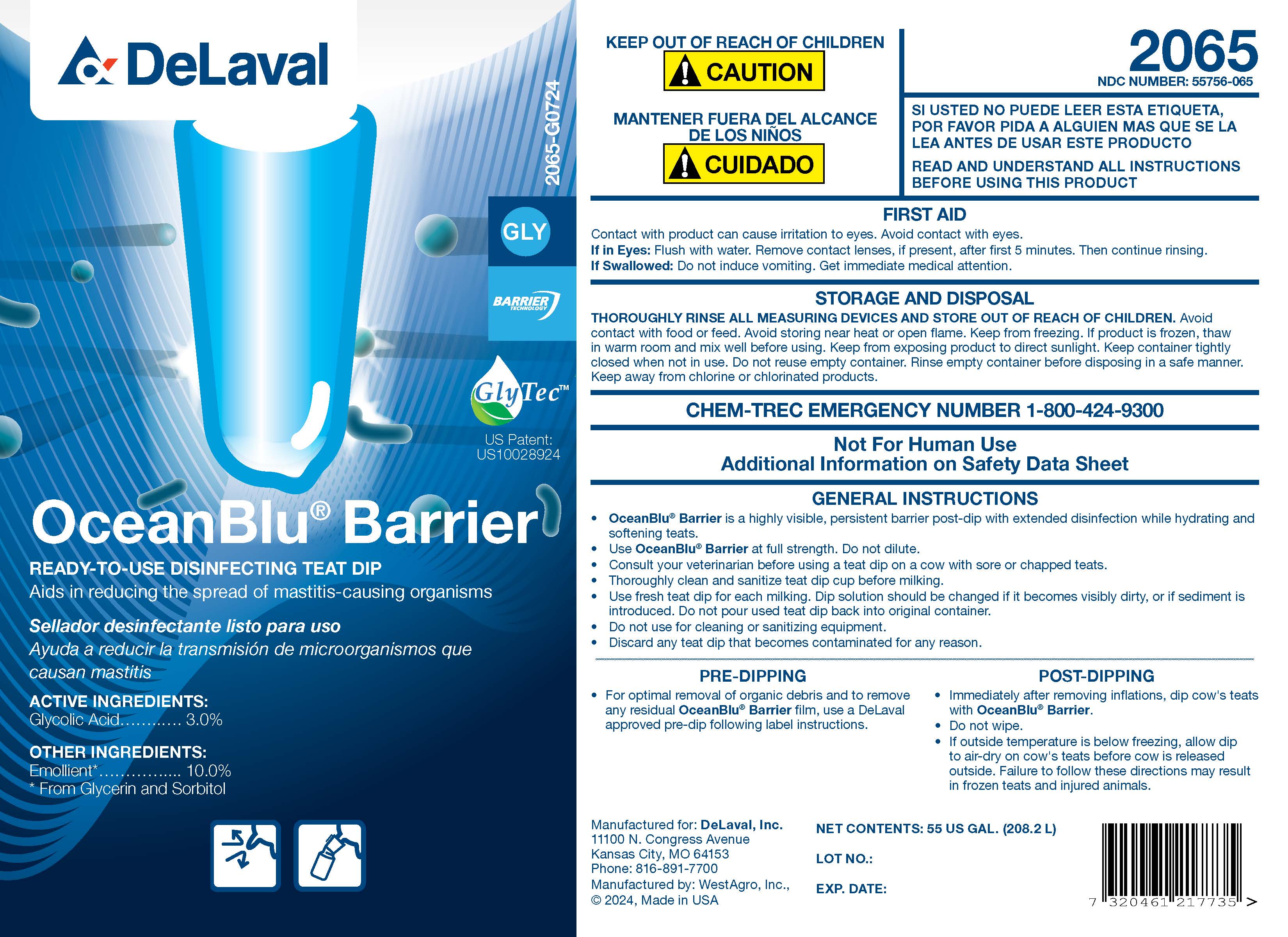 DRUG LABEL: OceanBlu Barrier
NDC: 55756-065 | Form: SOLUTION
Manufacturer: DeLaval
Category: animal | Type: OTC ANIMAL DRUG LABEL
Date: 20240925

ACTIVE INGREDIENTS: GLYCOLIC ACID 30.4 g/1 L
INACTIVE INGREDIENTS: GLYCERIN; XANTHAN GUM; POVIDONE K30; SORBITOL; C9-11 PARETH-8; FD&C BLUE NO. 1; SODIUM HYDROXIDE; WATER; 1-OCTANESULFONIC ACID; SODIUM C14-16 OLEFIN SULFONATE

DeLaval
OceanBlu® Barrier

PURPOSE

READY-TO-USE DISINFECTING TEAT DIP

Aids in reducing the spread of mastitis-causing organisms

ACTIVE INGREDIENTS:

Glycolic Acid ................ 3.0%

INACTIVE INGREDIENTS:

Emollient* ............... 10.0%

* From Glycerin and Sorbitol

GlyTecTM

US Patent: US10028924

2065-G0724

GLY

Barrier Technology

KEEP OUT OF REACH OF CHILDREN

!CAUTION

MANTENER FUERA DEL ALCANCE DE LOST NINOS

!CUIDADO

2065

NDC NUMBER 55756-065

SI USTED NO PUEDE LEER ESTA ETIQUETA, POR FAVOR PIDA A ALGUIEN MAS QUE SE LA LEA ANTES DE USAR ESTE PRODUCTO

READ AND UNDERSTAND ALL INSTRUCTIONS BEFORE USING THIS PRODUCT

FIRST AID

Contact with product can cause irritation to eyes. Avoid contact with eyes.

If In Eyes: Flush with water. Remove contact lenses, if present, after first 5 minutes. Then continue rinsing.

If Swallowed: Do not induce vomiting. Get immediate medical attention.

STORAGE AND DISPOSAL

THOROUGHLY RINSE ALL MEASURING DEVICES AND STORE OUT OF REACH OF CHILDREN. Avoid contact with food or feed. Avoid storing near heat or open flame. Keep from freezing. If product is frozen, thaw in warm room and mix well before using. Keep from exposing product to direct sunlight. Keep container tightly closed when not in use. Do not reuse empty container. Rinse container before disposing in a safe manner. Keep away from chlorine and chlorinated products.

CHEM-TREC EMERGENCY NUMBER 1-800-424-9300

Not For Human Use

Additional Information on Safety Data Sheet

GENERAL INSTRUCTIONS

- OceanBlu® Barrier is a highly visible, persistent barrier post-dip with extended disinfection while hydrating and softening teats.
- Use OceanBlu® Barrier at full strength. Do not dilute.
- Consult your veterinarian before using a teat dip on a cow with sore or chapped teats.
- Thoroughly clean and sanitize teat dip cup before milking.
- Use fresh teat dip for each milking. Dip solution should be changed if it becomes visibly dirty, or if sediment is introduced. Do not pour used teat dip back into original container.
- Do not use for cleaning or sanitizing equipment.
- Discard any teat dip that becomes contaiminated for any reason.

PRE-DIPPING

- For optimal removal of organic debris and to remove any residual OceanBlu® Barrier film, use a DeLaval approved pre-dip following label instructions.

POST-DIPPING

- Immediately after removing inflations, dip cow's teats with OceanBlu® Barrier.
- Do not wipe.
- If outside temperature is below freezing, allow dip to air-dry on cow's teats before cow is released outside. Failure to follow these directions may result in frozen teats and injured animals.

Manufactured for: DeLaval, Inc.
11100 N. Congress Avenue
Kansas City, MO 64153
Phone: 816-891-7700
Manufactured by: WestAgro, Inc.,
©2024, Made in USA

NET CONTENTS:

LOT NO.:

EXP. DATE:

PACKAGE LABEL

Add image transcription here...